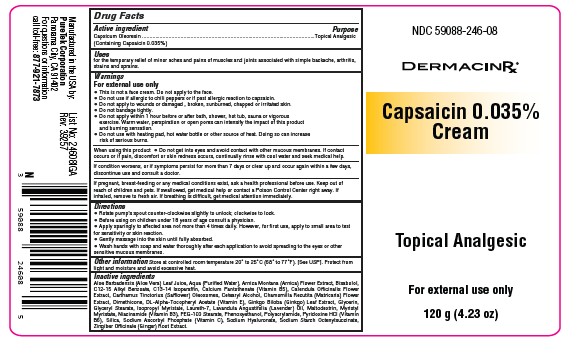 DRUG LABEL: Capsaicin 0.035% Cream
NDC: 59088-246 | Form: CREAM
Manufacturer: Puretekcorp
Category: otc | Type: HUMAN OTC DRUG LABEL
Date: 20250820

ACTIVE INGREDIENTS: CAPSAICIN 0.35 mg/1 g
INACTIVE INGREDIENTS: BISABOLOL; C12-15 ALKYL BENZOATE; .ALPHA.-TOCOPHEROL ACETATE, DL-; ISOPROPYL MYRISTATE; LAVANDULA ANGUSTIFOLIA (LAVENDER) OIL; SODIUM ASCORBYL PHOSPHATE; SODIUM HYALURONATE; MALTODEXTRIN; GINGER; PHENOXYETHANOL; ALUMINUM STARCH OCTENYLSUCCINATE; PYRIDOXINE HCL; DIMETHICONE; C13-14 ISOPARAFFIN; CARTHAMUS TINCTORIUS (SAFFLOWER) OLEOSOMES; CALENDULA OFFICINALIS FLOWER; SILICA; ALOE BARBADENSIS LEAF JUICE; AQUA; GLYCERIN; CALCIUM PANTOTHENATE; GINKGO BILOBA LEAF; ARNICA MONTANA FLOWER; CETEARYL ALCOHOL; PEG-100 STEARATE; CHAMOMILE; GLYCERYL STEARATE; MYRISTYL MYRISTATE; ACRYLAMIDE/SODIUM ACRYLOYLDIMETHYLTAURATE COPOLYMER (120000 MPA.S AT 1%); NIACINAMIDE; LAURETH-7

Capsaicin 0.035% Cream 59088-246

Active ingridient

Capsaicin 0.035%

Purpose

Topical Analgesic

Uses

for the temporary relief of minor aches and pains of muscles and joints associated with simple backache, arthritis, strains and sprains.

Warnings

For external use only

• This is not a face cream. Do not apply to the face.
• Do not use if allergic to chili peppers or if past allergic reaction to capsaicin.
• Do not apply to wounds or damaged , broken, sunburned, chapped or irritated skin.
• Do not bandage tightly.
• Do not apply within 1 hour before or after bath, shower, hot tub, sauna or vigorous exercise. Warm water, perspiration or open pores can intensify the impact of this product and burning sensation.
• Do not use with heating pad, hot water bottle or other source of heat. Doing so can increase risk of serious burns.

When using this product

Do not get into eyes and avoid contact with other mucous membranes. If contact occurs or if pain, discomfort or skin redness occurs, continually rinse with cool water and seek medical help.

STOP USE

If condition worsens, or if symptoms persist for more than 7 days or clear up and occur again within a few days, discontinue use and consult a doctor.

ASK DOCTOR

If pregnant, breast-feeding or any medical conditions exist, ask a health professional before use.

Keep out of reach of children and pets. If swallowed, get medical help or contact a Poison Control Center right away. If
inhaled, remove to fresh air. If breathing is difficult, get medical attention immediately.

Directions

• Rotate pump’s spout counter-clockwise slightly to unlock; clockwise to lock.
• Before using on children under 18 years of age consult a physician.
• Apply sparingly to affected area not more than 4 times daily. However, for first use, apply to small area to test for sensitivity or skin reaction.
• Gently massage into the skin until fully absorbed.
• Wash hands with soap and water thoroughly after each application to avoid spreading to the eyes or other sensitive mucous membranes.

Other Information

Store at controlled room temperature 20° to 25°C (68° to 77°F). [See USP]. Protect from light and moisture and avoid excessive heat.

Inactive ingredients

Aloe Barbadensis (Aloe Vera) Leaf Juice, Aqua (Purified Water), Arnica Montana (Arnica) Flower Extract, Bisabolol,
C12-15 Alkyl Benzoate, C13-14 Isoparaffin, Calcium Pantothenate (Vitamin B5), Calendula Officinalis Flower
Extract, Carthamus Tinctorius (Safflower) Oleosomes, Cetearyl Alcohol, Chamomilla Recutita (Matricaria) Flower
Extract, Dimethicone, DL-Alpha-Tocopheryl Acetate (Vitamin E), Ginkgo Biloba (Ginkgo) Leaf Extract, Glycerin,
Glyceryl Stearate, Isopropyl Myristate, Laureth-7, Lavandula Angustifolia (Lavender) Oil, Maltodextrin, Myristyl
Myristate, Niacinamide (Vitamin B3), PEG-100 Stearate, Phenoxyethanol, Polyacrylamide, Pyridoxine HCl (Vitamin
B6), Silica, Sodium Ascorbyl Phosphate (Vitamin C), Sodium Hyaluronate, Sodium Starch Octenylsuccinate,
Zingiber Officinale (Ginger) Root Extract.